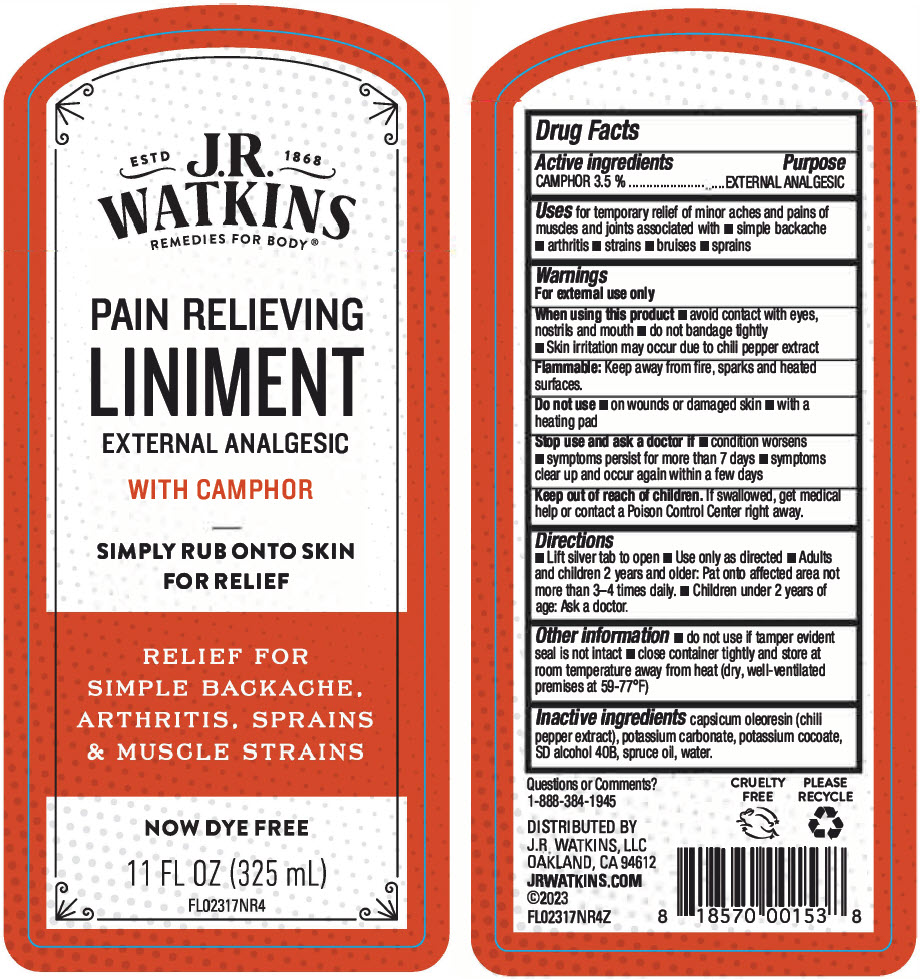 DRUG LABEL: Pain Relieving
NDC: 72342-040 | Form: LINIMENT
Manufacturer: J.R. Watkins, LLC.
Category: otc | Type: HUMAN OTC DRUG LABEL
Date: 20240208

ACTIVE INGREDIENTS: CAMPHOR (NATURAL) 3.5 g/100 mL
INACTIVE INGREDIENTS: WATER; ALCOHOL; PICEA MARIANA LEAF OIL; POTASSIUM COCOATE; CAPSICUM OLEORESIN; POTASSIUM CARBONATE

Pain Relieving Liniment

Drug Facts

Active Ingredients

CAMPHOR 3.5%

Purpose

EXTERNAL ANALGESIC

Uses

for temporary relief of minor aches and pains of muscles and joints associated with

- simple backache
- arthritis
- strains
- bruises
- sprains

Warnings

For external use only.

When using this product

- avoid contact with eyes, nostrils and mouth
- do not bandage tightly

Flammable:Keep away from fire, sparks and heated surfaces

Do not use

- on wounds or damaged skin
- with a heading pad

Stop use and ask a doctor if

- condition worsens
- symptoms persist for more than 7 days
- symptoms clear up and occur again within a few days

Keep out of reach of children.If swallowed, get medical help or contact a Poison Control Center right away.

Directions

- Lift silver tab to open
- Use only as directed
- Adults and children 2 years and older: Pat onto affected area not more than 3-4 times daily.
- Children under 2 years of age: Ask a doctor.

Other information

- do not use if tamper evident seal is not intact
- close container tightly and store at room temperature away from heat (dry, well-ventilated premises at 59-77°F)

Inactive ingredients

capsicum oleoresin (chili pepper extract), potassium carbonate, potassium cocoate, SD alcohol 40B, spruce oil, water

Questions or Comments?

1-888-384-1945

Do not use if tamper evident seal is not intact

DISTRIBUTED BY
J.R. WATKINS, LLC
Oakland, CA 94612

PRINCIPAL DISPLAY PANEL - 325 mL Bottle Label

ESTD
1868

J.R.
WATKINS
REMEDIES FOR BODY®

PAIN RELIEVING
LINIMENT
EXTERNAL ANALGESIC

WITH CAMPHOR

SIMPLY RUB ONTO SKIN
FOR RELIEF

RELIEF FOR
SIMPLE BACKACHE,
ARTHRITIS, SPRAINS
& MUSCLE STRAINS

NOW DYE FREE

11 FL OZ (325 mL)

FL02317NR4